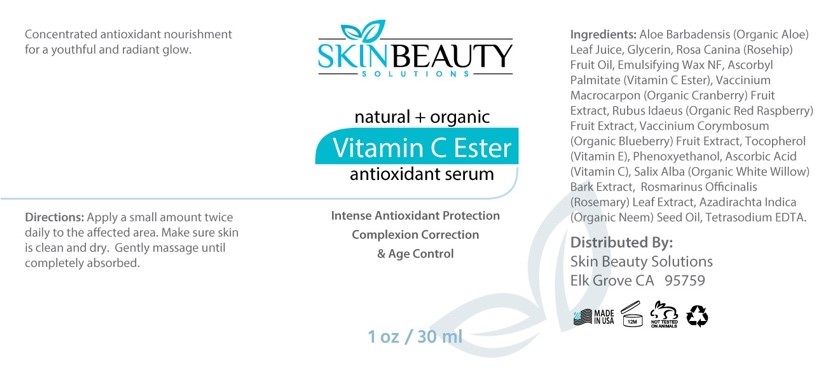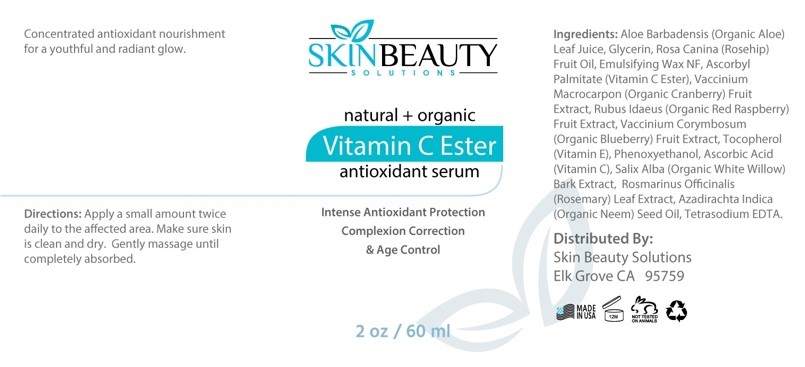 DRUG LABEL: Vitamin C Ester Serum
NDC: 84785-0007 | Form: SOLUTION
Manufacturer: Gazebo Wellness SKIN LLC
Category: otc | Type: HUMAN OTC DRUG LABEL
Date: 20241216

ACTIVE INGREDIENTS: CRANBERRY SEED 0.3 mg/30 mL; ALOE VERA LEAF 0.3 mg/30 mL; ROSEMARY 0.3 mg/30 mL; RASPBERRY 0.3 mg/30 mL; HIGHBUSH BLUEBERRY SEED OIL 0.3 mg/30 mL; WILLOW BARK 0.3 mg/30 mL; ASCORBIC ACID 0.3 mg/30 mL
INACTIVE INGREDIENTS: PHENOXYETHANOL; TETRASODIUM EDETATE DIHYDRATE; GLYCERIN; VITAMIN E POLYETHYLENE GLYCOL SUCCINATE

DOSAGE AND ADMINISTRATION

Concentrated antioxidant nourishment for a youthful and radiant glow.

WARNINGS

Apply a small amount twice daily to the affected area. Make sure skin is clean and dry. Gently massage until completely absorbed.

INACTIVE INGREDIENT

Inactive ingredients: Glycerin, Emulsifying Wax NF, Phenoxyethanol, Tetrasodium EDTA.

ACTIVE INGREDIENT

Active ingredients: Aloe Vera Leaf Juice, Rosehip Fruit Oil, Vitamin C Ester, Organic Cranberry Extract, Organic Red Raspberry Extract, Organic Blueberry Extract, Vitamin E, Ascorbic Acid, Organic White Willow Bark Extract, Rosemary Leaf Extract, Organic Neem Seed Oil.

INDICATIONS AND USAGE

Directions: Apply a small amount twice daily to the affected area. Make sure skin is clean and dry. Gently massage until completely absorbed.

keep out of reach of children

PURPOSE

natural + organic Vitamin C Ester antioxidant serum
Intense Antioxidant Protection Complexion Correction & Age Control

Distributed By:
Skin Beauty Solutions Elk Grove CA 95759

PACKAGE LABEL

Content of Labeling